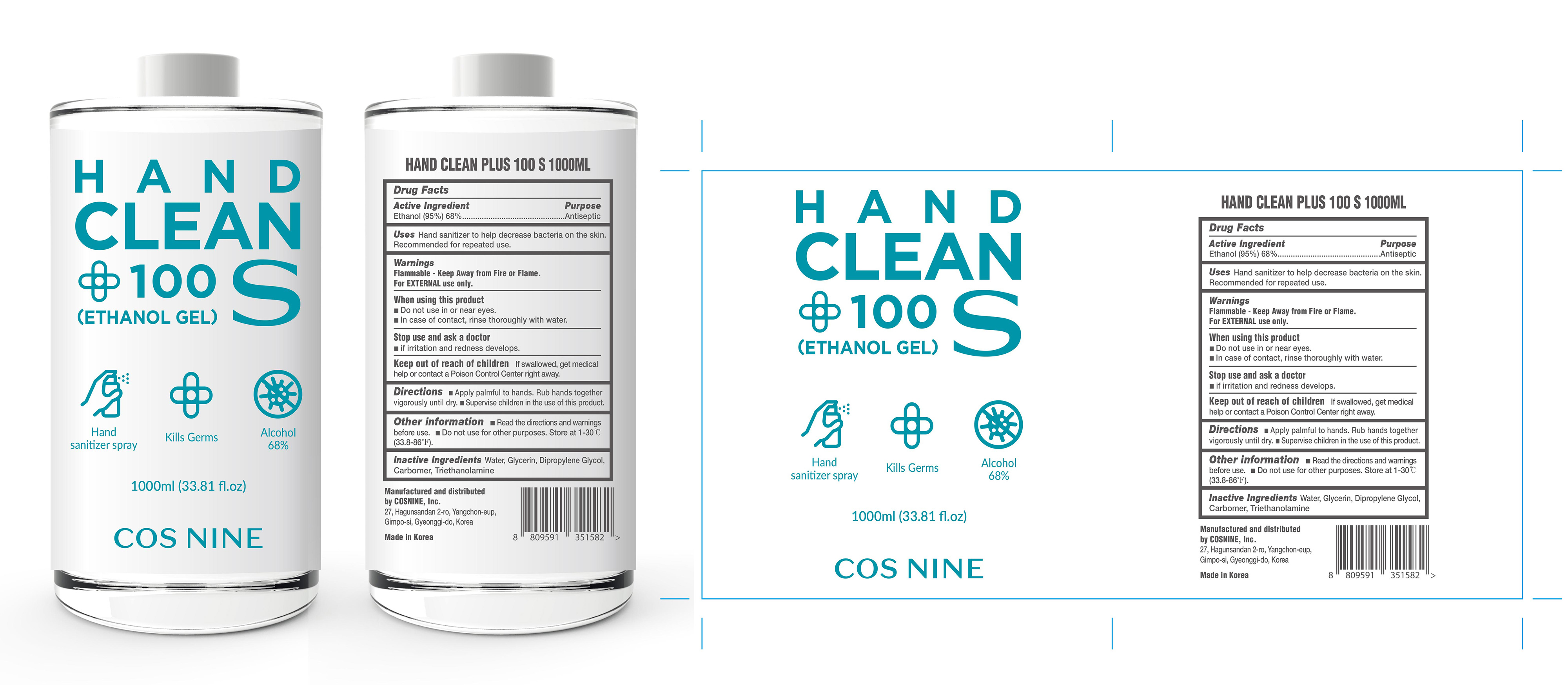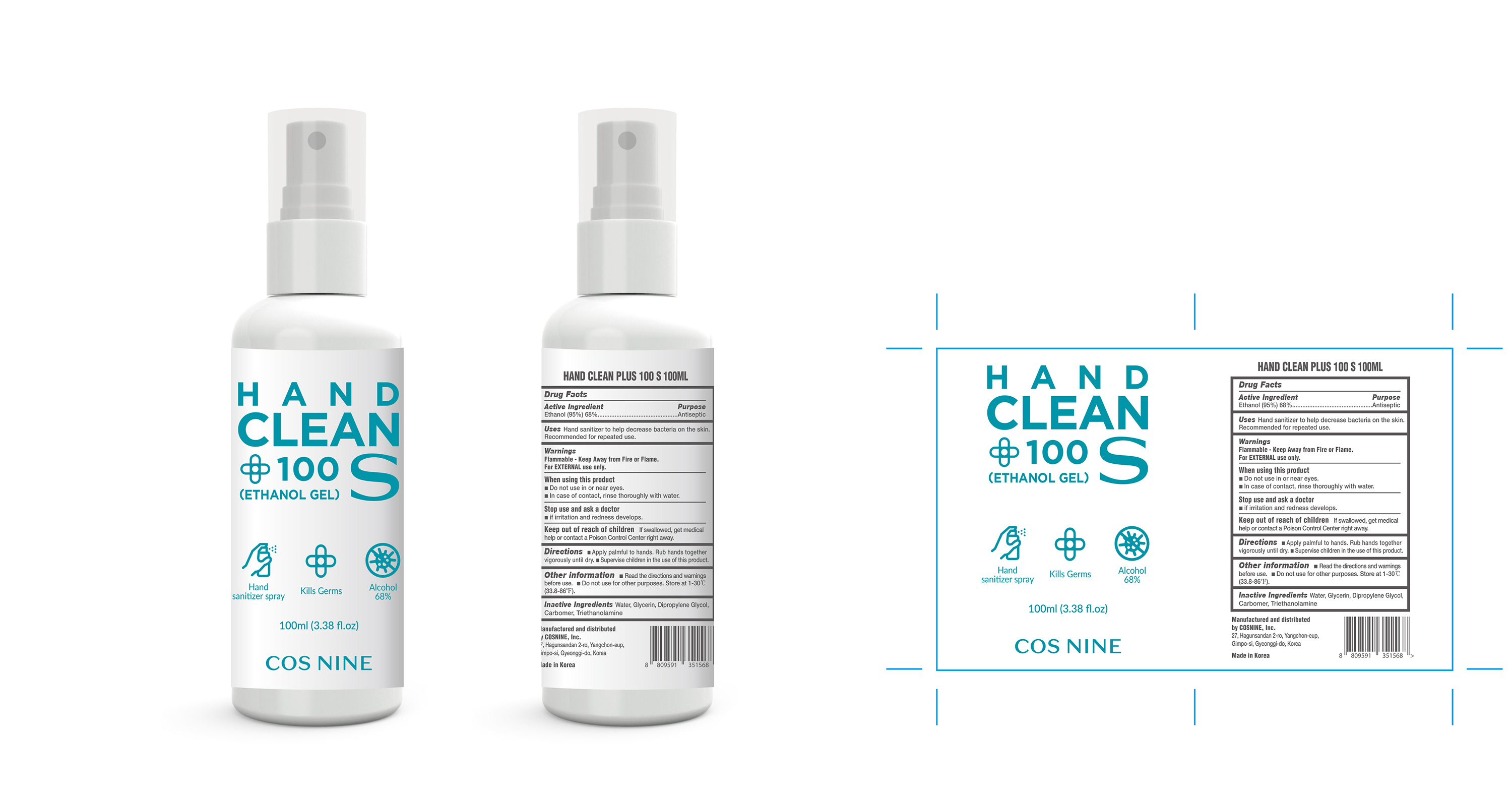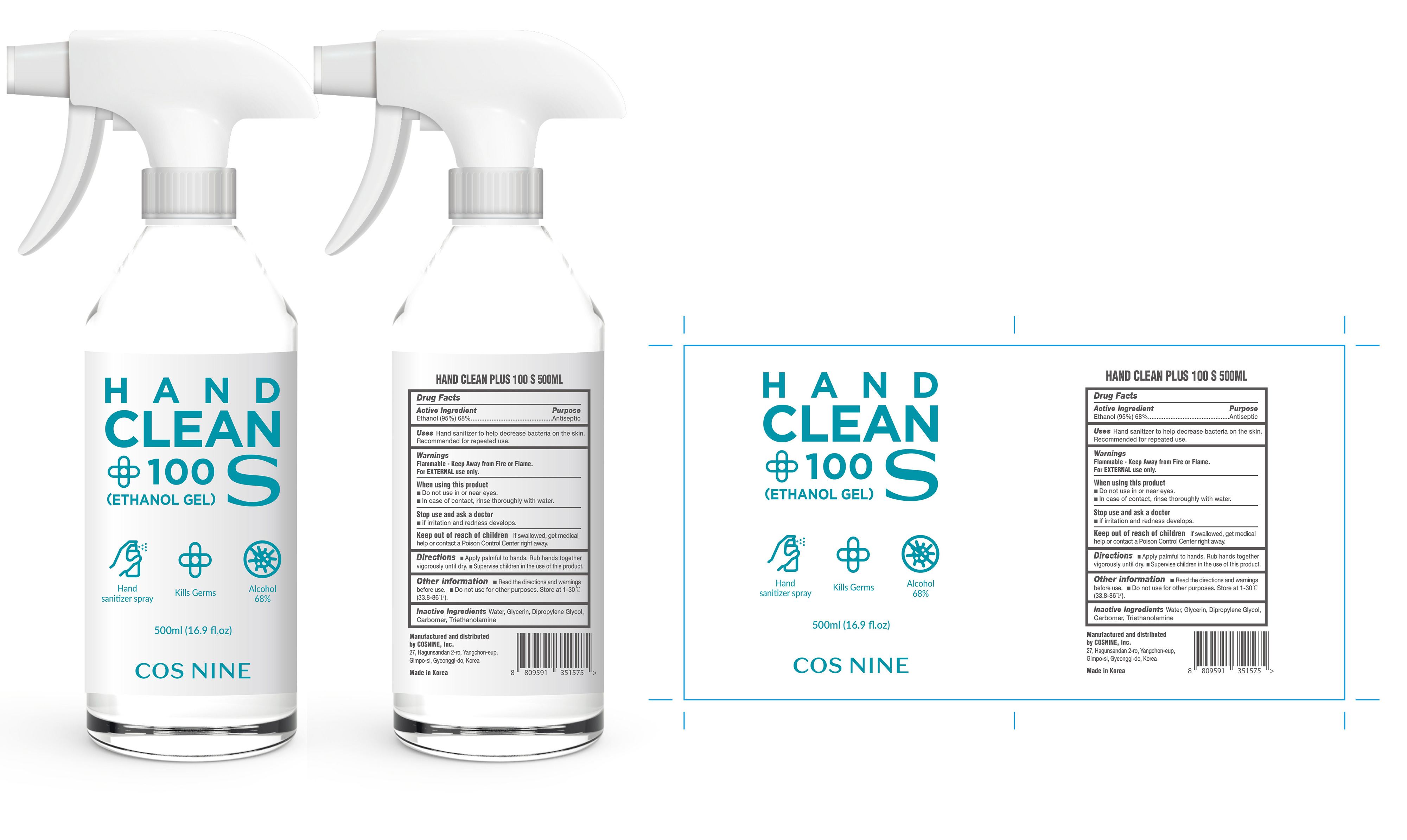 DRUG LABEL: Hand Clean Plus 100 S
NDC: 73330-0015 | Form: LIQUID
Manufacturer: COSNINE Inc
Category: otc | Type: HUMAN OTC DRUG LABEL
Date: 20200517

ACTIVE INGREDIENTS: ALCOHOL 0.68 mL/1 mL
INACTIVE INGREDIENTS: GLYCERIN; WATER; TROLAMINE; CARBOMER HOMOPOLYMER TYPE C (ALLYL PENTAERYTHRITOL CROSSLINKED); DIPROPYLENE GLYCOL

Active Ingredient

Ethanol (95%) 68%

Purpose

Antiseptic

Uses

Hand sanitizer to help decrease bacteria on the skin
Recommended for repeated use.

Warnings

For external use only.

Flammable - Keep away from fire or flame

When using this product

- Do not use in or near eyes.
- In case of contact, rinse thoroughly with water.

Stop use and ask a doctor

if irritation and redness develops.

Keep out of reach of children

if swallowed, get medical help or contact a Poison Control Center right away.

Directions

- Apply palmful to hands. Rub hands together vigorously until dry.
- Supervise children in the use of this product.

Other information

- Read the directions and warnings before use.
- Do not use for other purpose. Store at 1-30ºC (33.8-86ºF)

Inactive ingredients

Water, Glycerin, Dipropylene Glycol, Carbomer, Triethanolamine

Package Label - Principal Display Panel

1000 mL NDC: 73330-0015-1

500 mL NDC: 73330-0015-2

100 mL NDC: 73330-0015-3